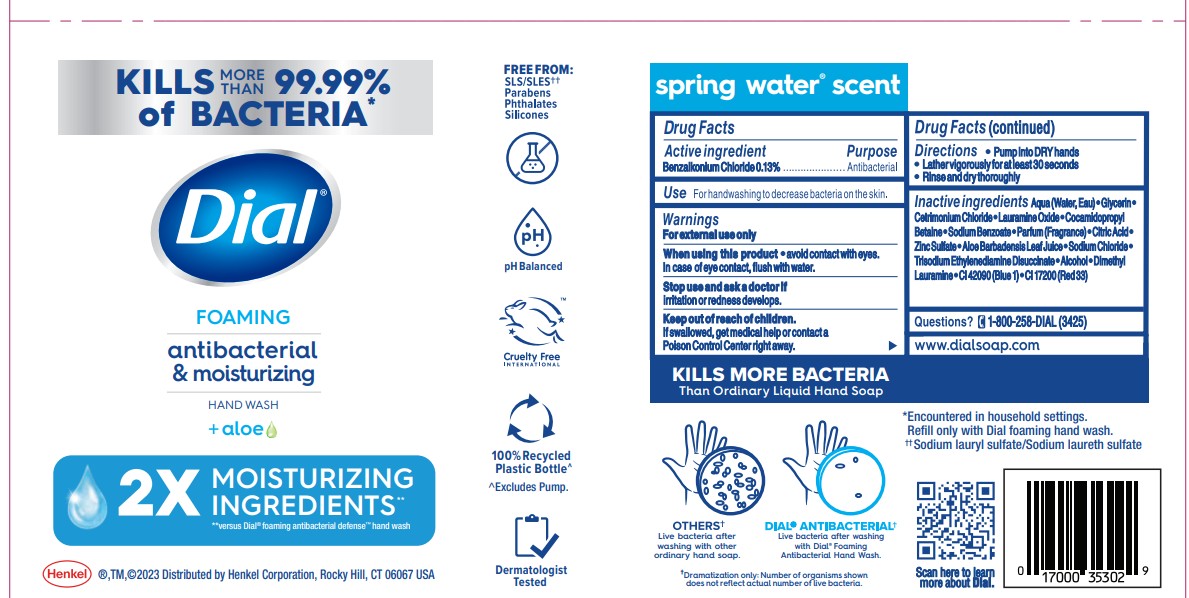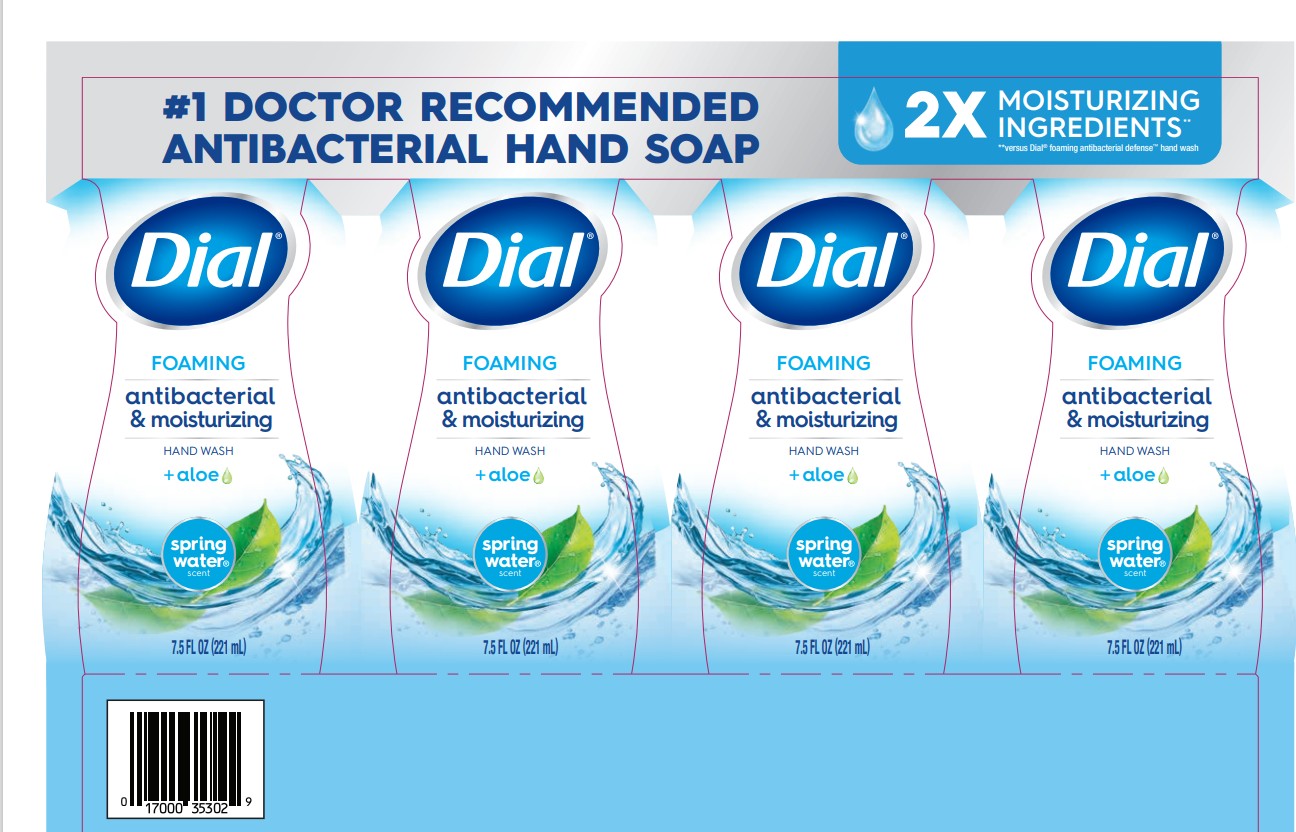 DRUG LABEL: Dial Foaming Antibacterial and Moisturizing Hand Wash Spring Water
NDC: 54340-016 | Form: SOLUTION
Manufacturer: Henkel Corporation
Category: otc | Type: HUMAN OTC DRUG LABEL
Date: 20251202

ACTIVE INGREDIENTS: BENZALKONIUM CHLORIDE 0.13 g/100 mL
INACTIVE INGREDIENTS: WATER 91.355 mL/100 mL

Dial Foaming Antibacterial & Moisturizing Hand Wash Spring Water

Active Ingredient

Benzalkonium Chloride 0.13%

Purpose

Antibacterial

Uses

For Handwashing to decrease bacteria on the skin.

WARNINGS

For external use only

When using this product

Avoid contact with eyes. In case of eye contact, flush with water.

Stop use and ask a doctor if

irritation or redness develops.

Keep out of reach of children

if swallowed, get medical help or contact a poison control center right away.

Directions

Directions . Pump into DRY hands
. Lather vigorously for at least 30 seconds
. Rinse and dry thoroughly

INACTIVE INGREDIENT

Spring Water

Aqua (Water, Eau)
Lauramidopropylamine Oxide
Cetrimonium Chloride
Lauramine Oxide
Glycerin
Citric Acid
Cocamidopropyl Betaine
Trideceth-9
Sodium Benzoate
Myristamidopropylamine Oxide
PEG-5 Isononanoate
Parfum (Fragrance)
Benzalkonium Chloride
Zinc Sulfate
Aloe Barbadensis Leaf Juice
Sodium Chloride
Dimethyl Lauramine
Trisodium Ethylenediamine Disuccinate
Alcohol
Dimethyl Myristamine
CI 42090 (Blue 1)
CI 17200 (Red 33)

Encountered in household settings

#Antibacterial Hand Soap

Questions

? 1-800-258-DIAL (3425)

Legal entity

Distributed by Henkel
Corporation, Rocky Hill CT 06067

INDICATIONS AND USAGE

Kills 99.99% bacteria.

For handwashing to decrease bacteria on the skin.

Topical

Foaming Hand wash